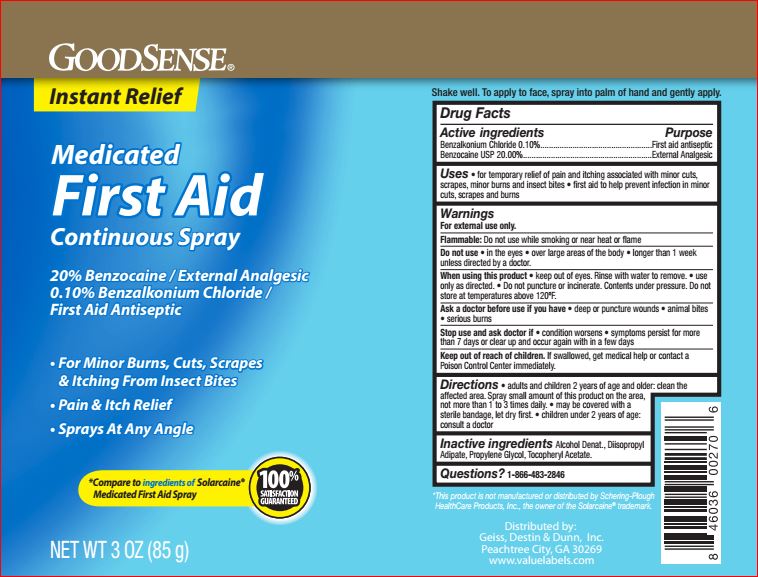 DRUG LABEL: Medicated First Aid
NDC: 50804-773 | Form: SPRAY
Manufacturer: Good Sense
Category: otc | Type: HUMAN OTC DRUG LABEL
Date: 20180607

ACTIVE INGREDIENTS: Benzalkonium Chloride 0.1 g/100 g; Benzocaine 20 g/100 g
INACTIVE INGREDIENTS: ALCOHOL; Diisopropyl Adipate; Propylene Glycol; .ALPHA.-TOCOPHEROL ACETATE

Drug Facts

Active ingredient Purpose
Benzocaine USP 20%.......................................External analgesic

Benzalkonium Chloride 0.1%...........................First Aid Antiseptic

Uses

Temporarily relieves pain and itching due to: • sunburn • minor burns • minor cuts • scrapes • insect bites • minor skin irritations• first aid to help prevent infection in minor cuts, scrapes, bites and burns

Warnings
For external use only.

Flammable: Do not use while smoking or near heat or flame Do not use in large quantities, particularly over raw surfaces or blistered areas
When using this product
• keep out of eyes
• do not apply over large areas of the body or in large quantites. in case of deep or puncture wounds, animal bites, or serious burns, concult a doctor
Stop use and ask doctor if
• condition gets worse • symptoms last more than 7 days
• symptoms clear up and occur again in a few days

•do not use longer than 1 week unless directed by doctor

Keep out of reach of children. If swallowed, get medical help or contact a Poison Control Center right away

DOSAGE AND ADMINISTRATION

- Directions • adults and children 2 years of age and older: apply to affected area not more than 1 to 3 times daily • may be covered with sterile bandage, let dry first children• under 2 years of age: ask a doctor

Inactive Ingredients:
Alcohol Denat.
Diisopropyl Adipate
Propylene Glycol
Tocopheryl Acetate